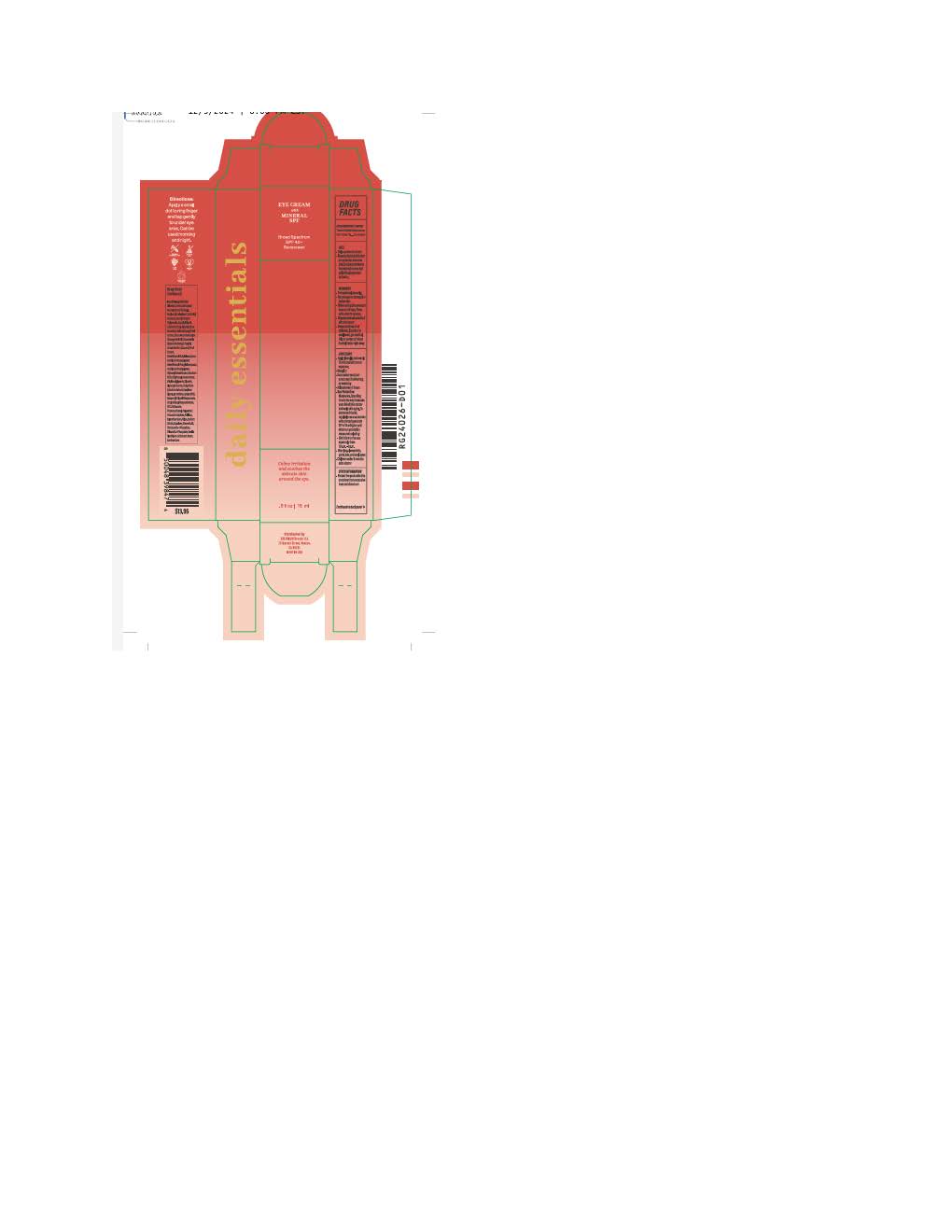 DRUG LABEL: Daily Essential Eye Cream
NDC: 84891-2409 | Form: LOTION
Manufacturer: Solarium Brands LLC
Category: otc | Type: HUMAN OTC DRUG LABEL
Date: 20251117

ACTIVE INGREDIENTS: ZINC OXIDE 9.7 mg/1 mL; TITANIUM DIOXIDE 19.4 mg/1 mL
INACTIVE INGREDIENTS: GLYCERIN; NEOPENTYL GLYCOL DIHEPTANOATE; GLYCERYL STEARATE SE; ALKYL (C12-15) BENZOATE; ALLANTOIN; CAPRYLYL GLYCOL; AVENA SATIVA WHOLE; DISODIUM EDTA-COPPER; BUTYLOCTYL SALICYLATE; TRICETEARETH-4 PHOSPHATE; PULLULAN; XANTHAN GUM; STEARETH-20; HEXYLENE GLYCOL; TRILAURETH-4 PHOSPHATE; OCTYLDODECYL NEOPENTANOATE; CETYL ALCOHOL; SQUALANE; POLYESTER-7; PEG-75 STEARATE; PHENOXYETHANOL; .ALPHA.-BISABOLOL, (+)-; ETHYLHEXYLGLYCERIN; DIMETHICONOL/PROPYLSILSESQUIOXANE/SILICATE CROSSPOLYMER (450000000 MW); LECITHIN, SOYBEAN; SILICON DIOXIDE; ETHYLHEXYL ISONONANOATE; CETETH-20; POTASSIUM SORBATE; WATER; FERRIC OXIDE YELLOW; FERROSOFERRIC OXIDE; COCOS NUCIFERA (COCONUT) FRUIT; FERRIC OXIDE RED; CITRUS AURANTIUM DULCIS (ORANGE) PEEL OIL; HEDYCHIUM SPICATUM ROOT; DIPHENYL DIMETHICONE (100 CST); SODIUM CITRATE; CAPRYLIC/CAPRIC TRIGLYCERIDE; SCLEROTIUM GUM; CITRUS NOBILIS (MANDARIN ORANGE) PEEL OIL

Daily Essential Eye Cream